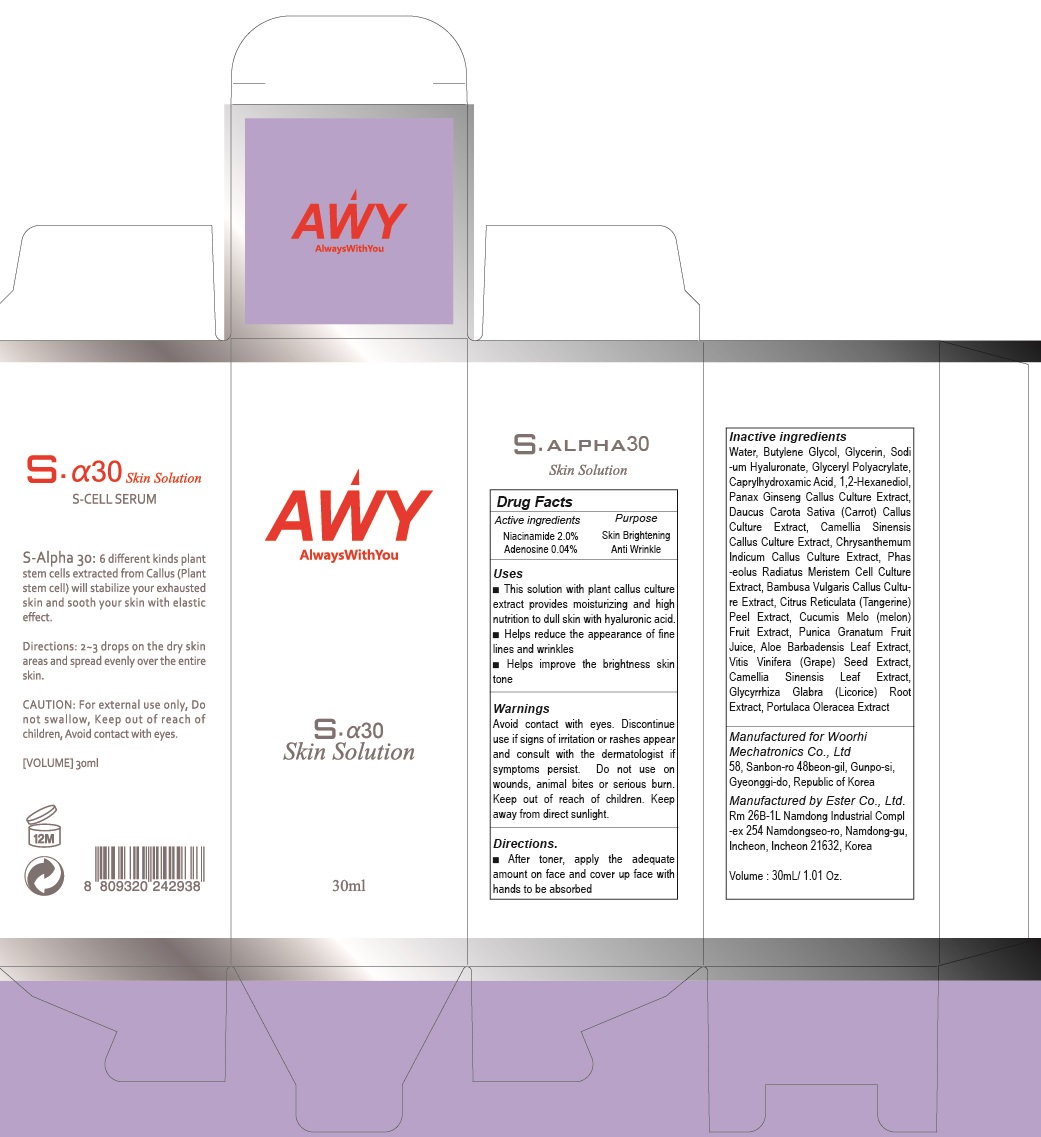 DRUG LABEL: S ALPHA 30 Skin
NDC: 72729-020 | Form: SOLUTION
Manufacturer: Woorhi Mechatronics Co., Ltd.
Category: otc | Type: HUMAN OTC DRUG LABEL
Date: 20181203

ACTIVE INGREDIENTS: Niacinamide 0.60 g/30 mL; Adenosine 0.012 g/30 mL
INACTIVE INGREDIENTS: Water; Butylene Glycol

ACTIVE INGREDIENT

Active Ingredient: Niacinamide 2.0%, Adenosine 0.04%

INACTIVE INGREDIENT

Inactive ingredients:

Water, Butylene Glycol, Glycerin, Sodium Hyaluronate, Glyceryl Polyacrylate, Caprylhydroxamic Acid, 1,2-Hexanediol, Panax Ginseng Callus Culture Extract, Daucus Carota Sativa (Carrot) Callus Culture Extract, Camellia Sinensis Callus Culture Extract, Chrysanthemum Indicum Callus Culture Extract, Phaseolus Radiatus Meristem Cell Culture Extract, Bambusa Vulgaris Callus Culture Extract, Citrus Reticulata (Tangerine) Peel Extract, Cucumis Melo (melon) Fruit Extract, Punica Granatum Fruit Juice, Aloe Barbadensis Leaf Extract, Vitis Vinifera (Grape) Seed Extract, Camellia Sinensis Leaf Extract, Glycyrrhiza Glabra (Licorice) Root Extract, Portulaca Oleracea Extract

PURPOSE

Purpose: Skin Brightening, Anti Wrinkle

WARNINGS

Avoid contact with eyes.

Discontinue use if signs of irritation or rashes appear and consult with the dermatologist if symptoms persist.

Do not use on wounds, animal bites or serious burn.

Keep out of reach of children.

Keep away from direct sunlight.

KEEP OUT OF REACH OF CHILDREN

Uses

■ This solution with plant callus culture extract provides moisturizing and high nutrition to dull skin with hyaluronic acid.

■ Helps reduce the appearance of fine lines and wrinkles

■ Helps improve writhe brightness skin tone

Directions

After toner, apply the adequate amount on face and cover up face with hands to be absorbed